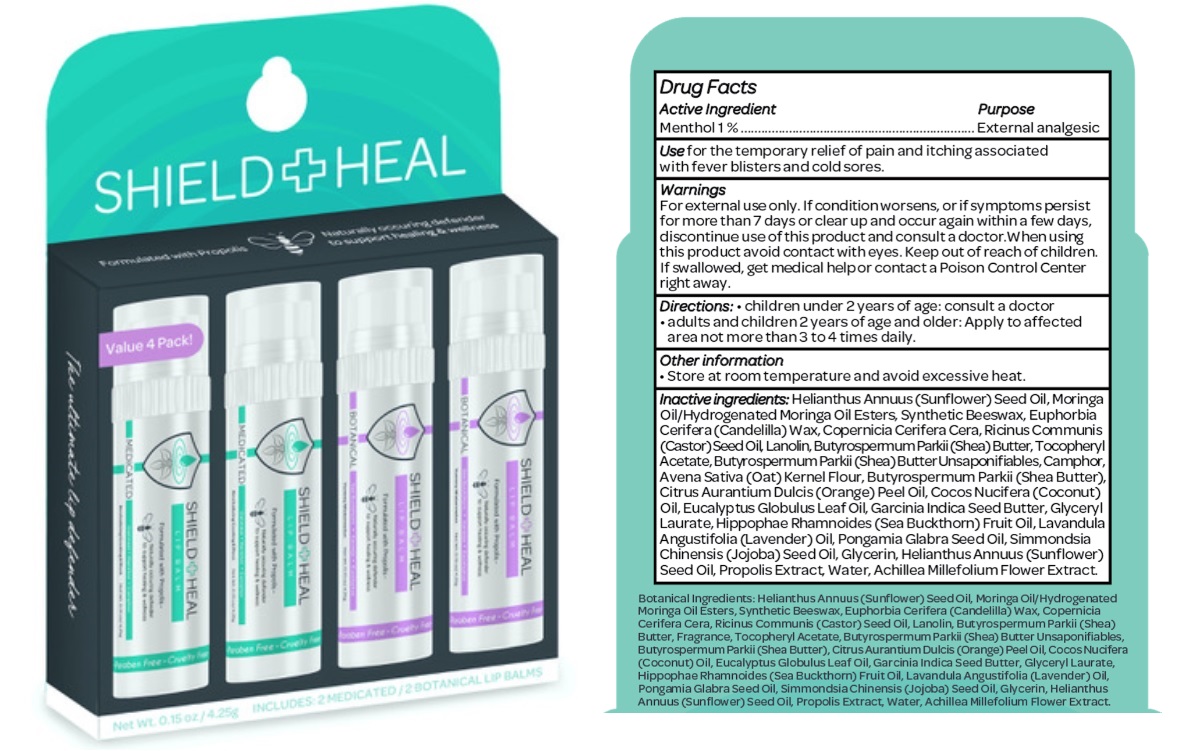 DRUG LABEL: Shield and Heal Lip Balm
NDC: 81470-002 | Form: KIT | Route: TOPICAL
Manufacturer: Shield and Heal Inc.
Category: otc | Type: HUMAN OTC DRUG LABEL
Date: 20230427

ACTIVE INGREDIENTS: MENTHOL 10 mg/1 g
INACTIVE INGREDIENTS: SYNTHETIC BEESWAX; CARNAUBA WAX; SHEA BUTTER; BUTYROSPERMUM PARKII (SHEA) BUTTER UNSAPONIFIABLES; OATMEAL; ORANGE OIL; COCONUT OIL; KARUM SEED OIL; GARCINIA INDICA SEED BUTTER; LAVENDER OIL; GLYCERIN; WATER; CASTOR OIL; GLYCERYL LAURATE; SUNFLOWER OIL; LANOLIN; CAMPHOR (SYNTHETIC); EUCALYPTUS OIL; .ALPHA.-TOCOPHEROL ACETATE; CANDELILLA WAX; ACHILLEA MILLEFOLIUM FLOWER; HIPPOPHAE RHAMNOIDES FRUIT OIL; JOJOBA OIL; PROPOLIS WAX

Shield + Heal Lip Balm Kit

Active ingredient

Menthol 1%

Purpose

External analgesic

Use

for the temporary relief of pain and itching associated with fever blisters and cold sores.

Warnings

For external use only.

If condition worsens, or if symptoms persist for more than 7 days or clear up and occur again within a few days, discontinue use of this product and consult a doctor.

When using this product

avoid contact with eyes.

Keep out of reach of children.

If swallowed, get medical help or contact a Poison Control Center right away.

Directions

- children under 2 years of age: consult a doctor.
- adults and children 2 years of age and older: Apply to affected area not more than 3 to 4 times daily

Other information

- Store at room temperature and avoid excessive heat.

Inactive ingredients

Helianthus Annuus (Sunflower) Seed Oil, Moringa Oil/Hydrogenated Moringa Oil Esters, Synthetic Beeswax, Euphorbia Cerifera (Candelilla) Wax, Copernicia Cerifera Cera, Ricinus Communis (Castor) Seed Oil, Lanolin, Butyrospermum Parkii (Shea) Butter, Tocopheryl Acetate, Butyrospermum Parkii (Shea) Butter Unsaponifiables, Camphor, Avena Sativa (Oat) Kernel Flour, Butyrospermum Parkii (Shea Butter), Citrus Aurantium Dulcis (Orange) Peel Oil, Cocos Nucifera (Coconut) Oil, Eucalyptus Globulus Leaf Oil, Garcinia Indica Seed Butter, Glyceryl Laurate, Hippophae Rhamnoides (Sea Buckthorn) Fruit Oil, Lavandula Angustifolia (Lavender) Oil, Pongamia Glabra Seed Oil, Simmondsia Chinensis (Jojoba) Seed Oil, Glycerin, Helianthus Annuus (Sunflower) Seed Oil, Propolis Extract, Water, Achillea Millefolium Flower Extract.